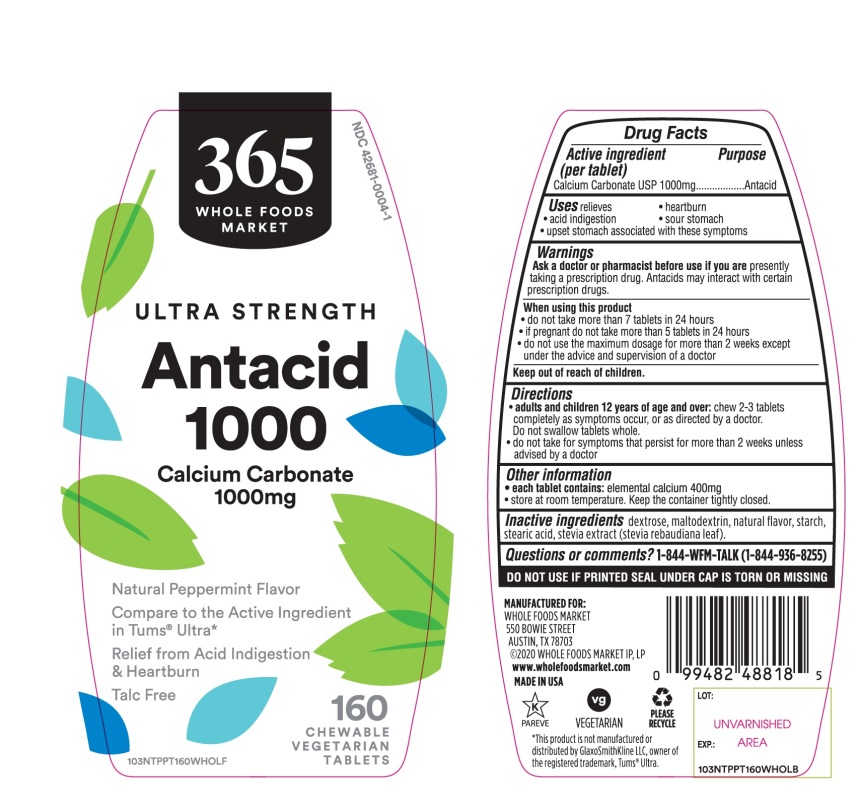 DRUG LABEL: WHOLE FOODS MARKET Health Ultra Strength Natural Antacid

NDC: 42681-0004 | Form: TABLET, CHEWABLE
Manufacturer: WHOLE FOODS MARKET, INC.
Category: otc | Type: HUMAN OTC DRUG LABEL
Date: 20251015

ACTIVE INGREDIENTS: CALCIUM CARBONATE 1000 mg/1 1
INACTIVE INGREDIENTS: DEXTROSE, UNSPECIFIED FORM; MALTODEXTRIN; STARCH, CORN; STEARIC ACID; STEVIA REBAUDIANA LEAF

WHOLE FOODS MARKET Ultra Strength Antacid Tablets

Active ingredient (per tablet)

Calcium Carbonate USP 1000mg

Purpose

Antacid

Uses

relieves

- heartburn
- acid indigestion
- sour stomach
- upset stomach associated with these symptoms

Warnings

Ask a doctor or pharmacist before use if you arepresently taking a prescription drug. Antacids may interact with certain prescription drugs.

When using this product

- do not take more than 7 tablets in 24 hours
- if pregnant do not take more than 5 tablets in 24 hours
- do not use the maximum dosage for more than 2 weeks except under the advice and supervision of a doctor.

Directions

- adults and children 12 years of age and over:chew 2-3 tablets as symptoms occur, or as directed by a doctor. Do not swallow tablets whole.
- do not take for symptoms that persist for more than 2 weeks unless advised by a doctor

Other information

- each tablet contains:elemental calcium 400mg
- store at room temperature. Keep the container tightly closed.

Inactive ingredients

dextrose, maltodextrin, natural flavors, starch, stearic acid, stevia extract (stevia rebaudiana leaf).

Questions or comments?

1-844-WFM-TALK (1-844-936-8255)

SAFETY SEALED: DO NOT USE IF PRINTED SEAL UNDER CAP IS TORN OR MISSING

Package/Label Principal Display Panel

36 WHOE FOODS MARKET

ULTRA STRENGTH

Antacid

1000

Calcium Carbonate 1000 mg

Natural Peppermint Flavor

ULTRA STRENGTH FORMULA

Compare to the Active Ingredient in Tums® Ultra*

Relief from Acid Indigestion & Heartburn

Talc Free

MANUFACTURED FOR:WHOLE FOODS MARKET 550 BOWIES STREETAUSTIN, TX 78703@2019 WHOLE FOODS MARKET IP, LP

www.wholefoodsmarket.com

MADE IN USA

160 CHEWABLE VEGETARIAN TABLETS

K PAREVE vg VEGETARIAN PLEASE RECYCLE

GLUTEN- FREE

*This product is not manufactured or distributed by GlaxoSmithKline LLC, owner of the registered trademark, Tums® Ultra.